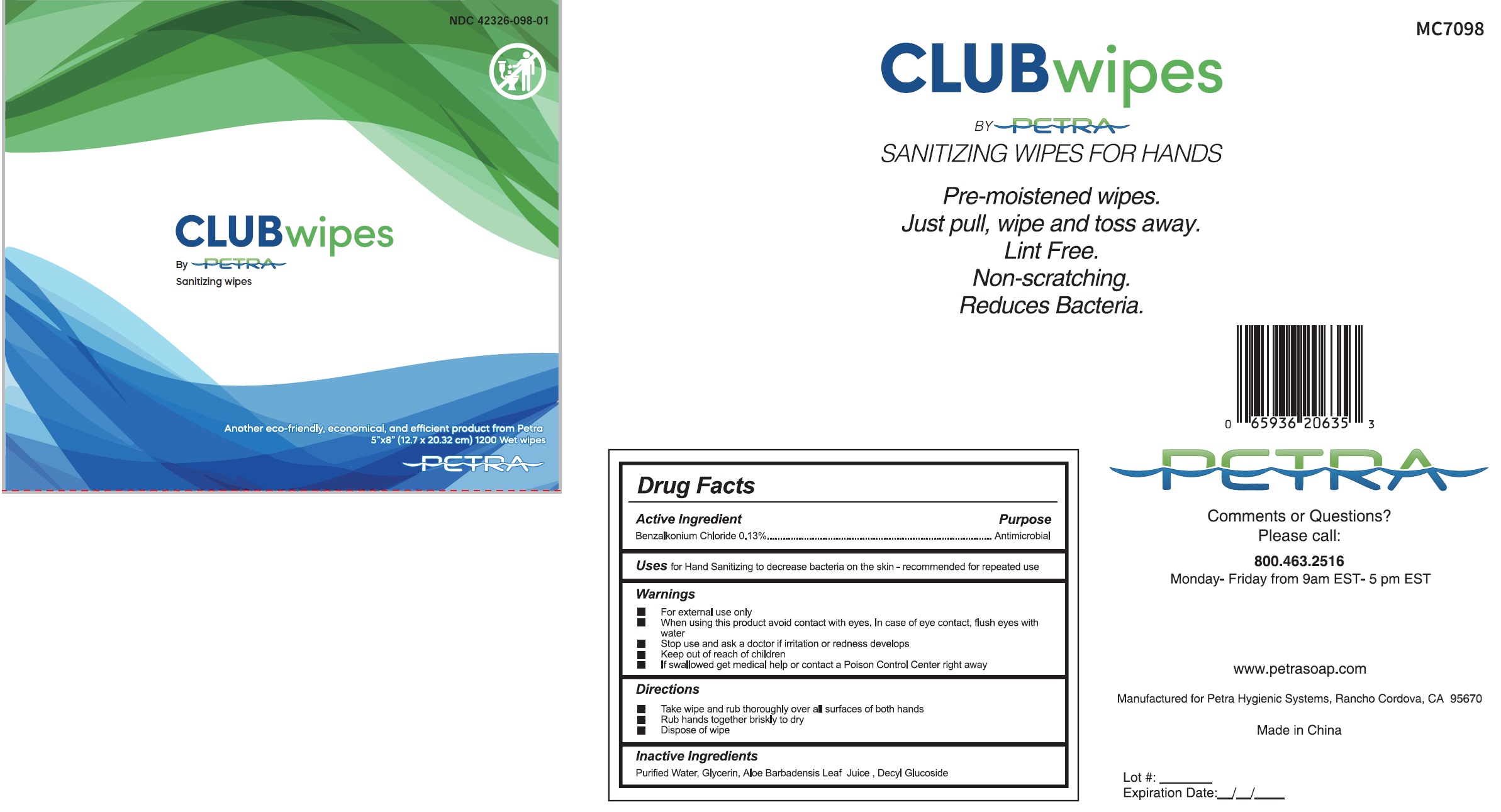 DRUG LABEL: Club Wipes Alcohol Free Antimicrobial Cleaning Wipes
NDC: 42326-098 | Form: SWAB
Manufacturer: Petra Hygienic Systems Int Ltd
Category: otc | Type: HUMAN OTC DRUG LABEL
Date: 20250717

ACTIVE INGREDIENTS: BENZALKONIUM CHLORIDE 1.3 mg/1 mL
INACTIVE INGREDIENTS: WATER; GLYCERIN; ALOE VERA LEAF; DECYL GLUCOSIDE

Club Wipes Alcohol Free Antimicrobial Cleaning Wipes

Active Ingredient

Benzalkonium Chloride 0.13%

Purpose

Antimicrobial

Uses

for Hand Sanitizing to decrease bacteria on the skin - recommended for repeated use

Warnings

- For external use only

• When using this product

avoid contact with eyes. In case of eye contact, flush eyes with water

• Stop use and ask a doctor

if irritation or redness develops

• Keep out of reach of children.

If swallowed get medical help or contact a Poison Control Center right away

Directions

- Take wipe and rub thoroughly over all surfaces of both hands
- Rub hands together briskly to dry
- Dispose of wipe

Inactive Ingredients

Purified Water, Glycerin, Aloe Barbadensis Leaf Juice, Decyl Glucoside